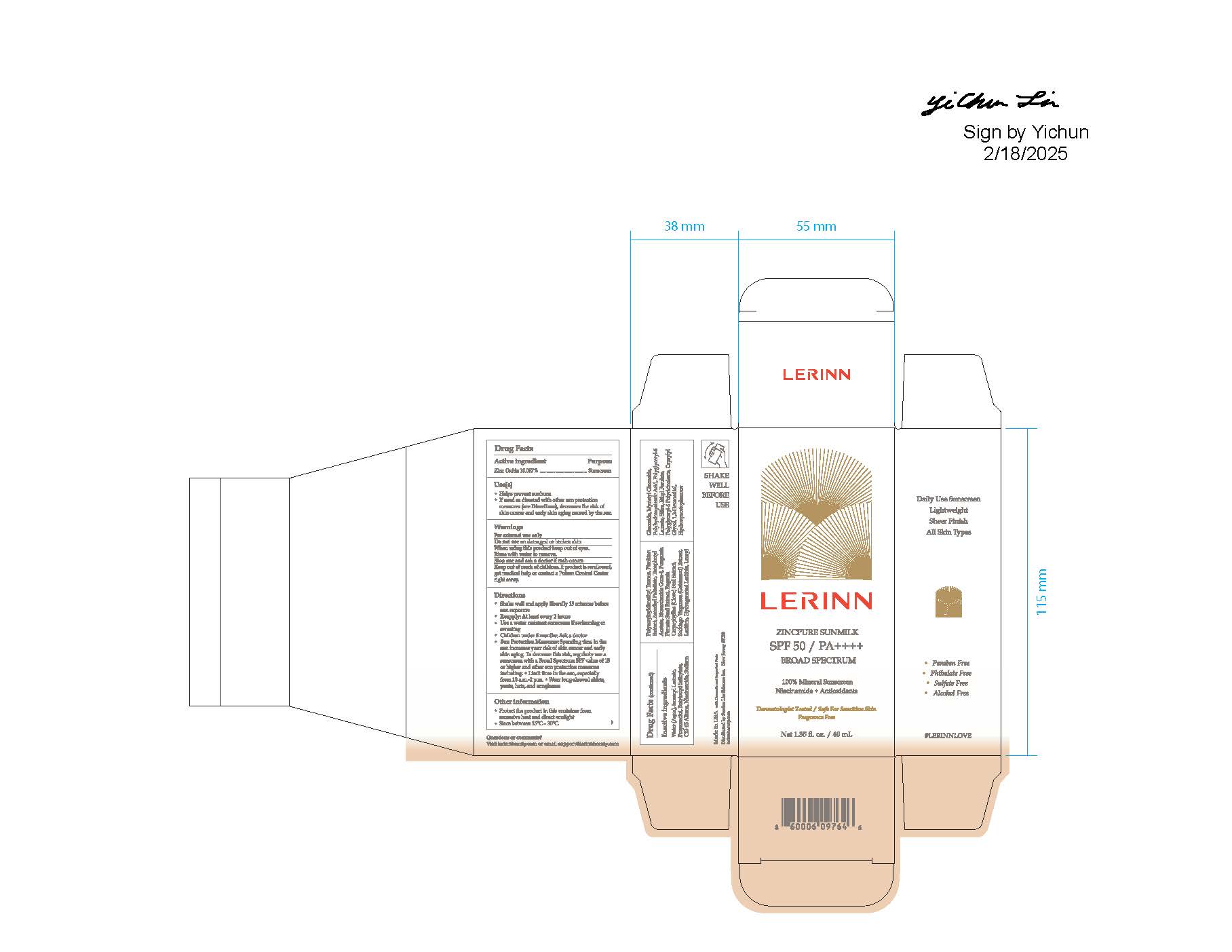 DRUG LABEL: LERINN ZINCPURE SUNMILK SPF 50
NDC: 85535-001 | Form: CREAM
Manufacturer: Serrina Lin Skincare Inc
Category: otc | Type: HUMAN OTC DRUG LABEL
Date: 20250410

ACTIVE INGREDIENTS: ZINC OXIDE 10 mg/1 mL
INACTIVE INGREDIENTS: HYDROXYACETOPHENONE; 1,2-HEXANEDIOL; CAPRYLYL GLYCOL; ETHYL FERULATE; SILICON DIOXIDE; ISOAMYL LAURATE; PROPANEDIOL; C13-15 ALKANE; BUTYLOCTYL SALICYLATE; NIACINAMIDE; SODIUM POLYACRYLOYLDIMETHYL TAURATE; ASCORBYL PALMITATE; .ALPHA.-TOCOPHEROL ACETATE, D-; BIOSACCHARIDE GUM-4; PONGAMIA PINNATA SEED; EUGENIA CARYOPHYLLUS (CLOVE) BUD OIL; SOLIDAGO VIRGAUREA WHOLE; LECITHIN, SOYBEAN; HYDROGENATED SOYBEAN LECITHIN; LAURYL GLUCOSIDE; WATER; MYRISTYL GLUCOSIDE; POLYHYDROXYSTEARIC ACID (2300 MW); POLYGLYCERYL-6 POLYRICINOLEATE; POLYGLYCERYL-6 LAURATE

LERINN ZINCPURE SUNMILK SPF 50

Active ingredients

Zinc Oxide 10%

Purpose

Sunscreen

Uses

- helps prevent sunburn
- if used as directed with other sun protection measures (see) decreases the risk of skin cancer and early skin aging caused by the sun Directions

Warnings

- For external use only

Do not use

on damaged or broken skin

When using this product

keep out of eyes, rinse with water to remove

Stop use and ask a doctor

if rash occurs

Keep out of reach of children.

If swallowed, get medical help or contact a Poison Control Center right away

Directions

- shake well and apply liberally 15 minutes before sun exposure
- reapply: At least every 2 hours.
- Usa a water resistant sunscreen if swimmin or sweating
- Sun Protection Measures:
- Spending time in the sun increases your risk of skin cancer and early skin aging. To decrease the risk, regularly use a sunscreen with a Broad Spectrum SPF value of 15 or higher and other sun protection measures including:
- limit time in the sun, especially from 10 a.m. to 2 p.m.
- wear long-sleeved shirts, pants, hats, and sunglasses
- children under 6 months of age: Ask a doctor

Other information

- protect the product in this container from excessive heat and direct sunlight
- store below 15°C-30° C

Inactive ingredients

Water, Isoamyl Laurate, Propanediol, Butyloctyl Salicylate, C13-15 Alkane, Niacinamide, Sodium Polyacryloyldimethyl Taurate, Plankton Extract, Ascorbyl Palmitate, Tocopheryl Acetate, Biosaccharide Gum-4, Pongamia Pinnata Seed Extract, Eugenia Caryophyllus (Clove) Bud Extract, Solidago Virgaurea (Goldenrod) Extract, Lecithin, Hydrogenated Lecithin, Lauryl Glucoside, Myristyl Glucoside, Polyhydroxystearic Acid, Polyglyceryl-6 Laurate, Silica, Ethyl Ferulate, Polyglyceryl-6 Polyricinoleate, Capryly Glcyol, 1,2-Hexanediol, Hydroxyacetophenone